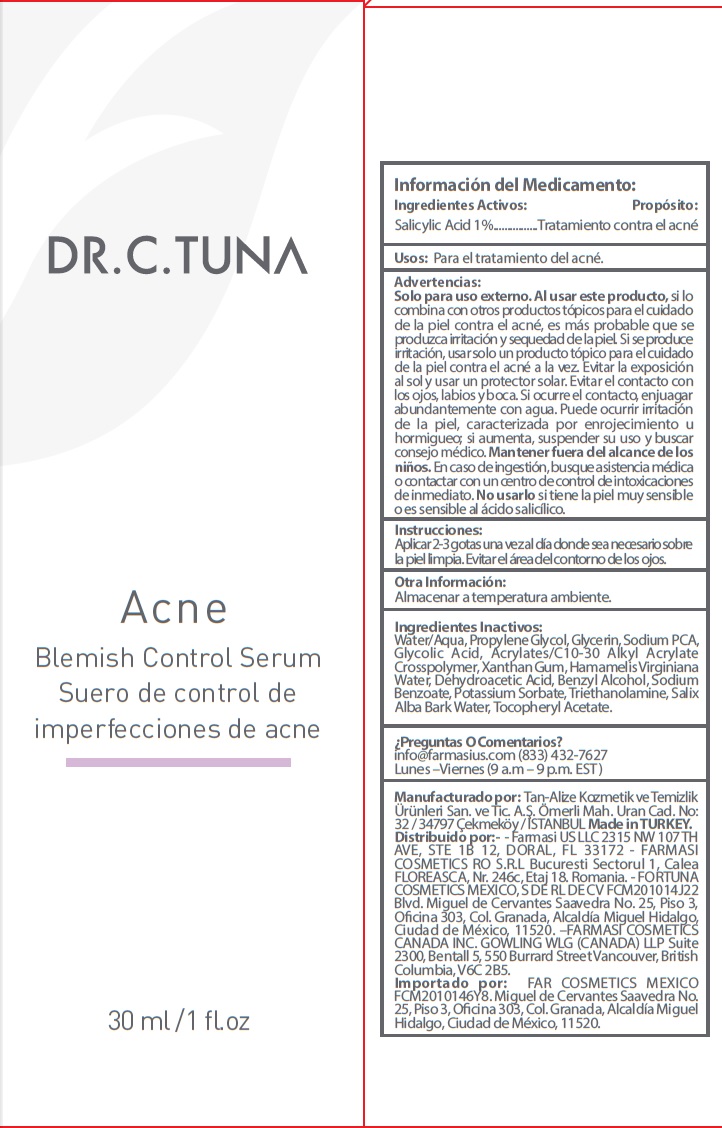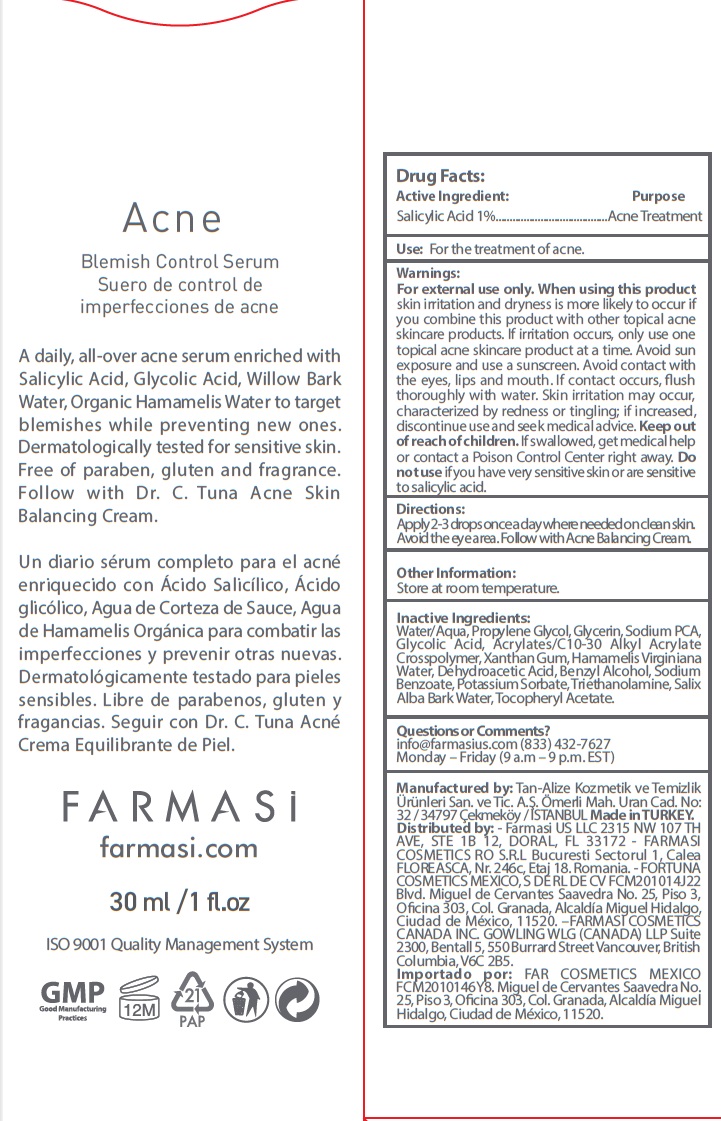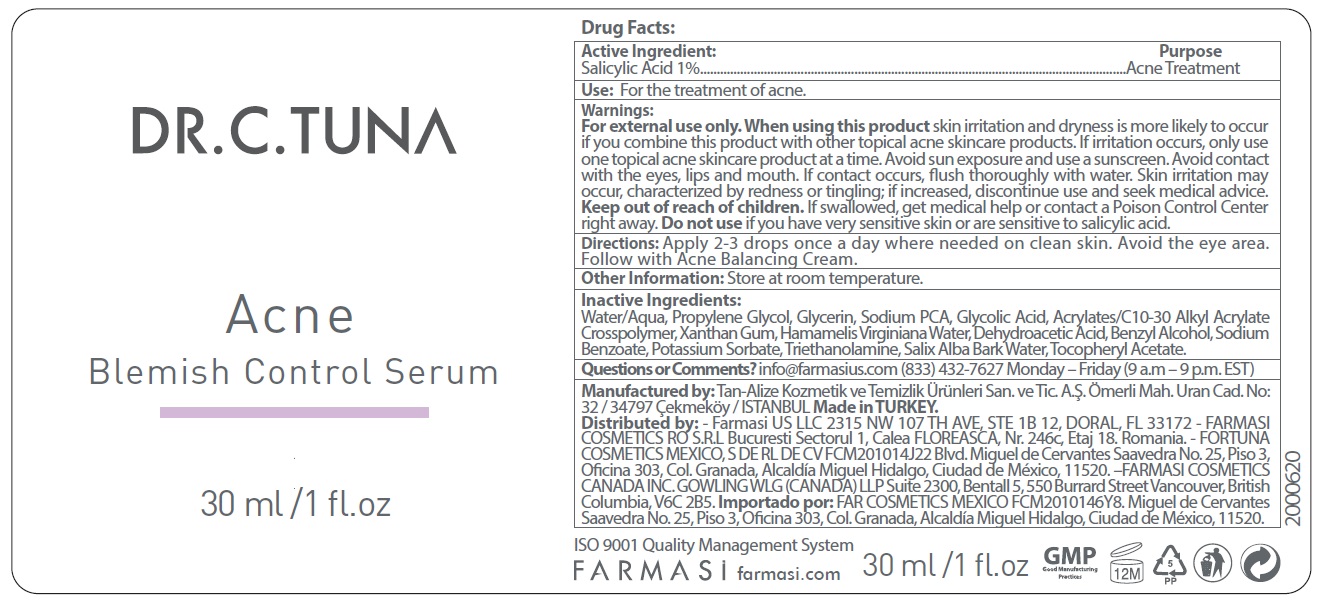 DRUG LABEL: Dr. C. Tuna Acne Blemish Control Serum
NDC: 74690-011 | Form: LIQUID
Manufacturer: Farmasi US LLC
Category: otc | Type: HUMAN OTC DRUG LABEL
Date: 20231105

ACTIVE INGREDIENTS: SALICYLIC ACID 10 mg/1 mL
INACTIVE INGREDIENTS: WATER; PROPYLENE GLYCOL; GLYCERIN; SODIUM PYRROLIDONE CARBOXYLATE; GLYCOLIC ACID; CARBOMER INTERPOLYMER TYPE A (ALLYL SUCROSE CROSSLINKED); XANTHAN GUM; DEHYDROACETIC ACID; BENZYL ALCOHOL; SODIUM BENZOATE; POTASSIUM SORBATE; TROLAMINE; SALIX ALBA BARK VOLATILE OIL; .ALPHA.-TOCOPHEROL ACETATE

Dr. C. Tuna Acne Blemish Control Serum

ACTIVE INGREDIENT

Salicylic Acid 1%

PURPOSE

Acne Treatment

USE

For the treatment of acne.

WARNINGS

For external use only

When using this product

skin irritation and dryness is more likely to occur if you combine this product with other topical acne skincare products. If irritation occurs, only use one topical acne skincare product at a time. Avoid sun exposure and use a sunscreen. Avoid contact with the eyes, lips and mouth. If contact occurs, flush thoroughly with water. Skin irritation may occur, characterized by redness or tingling; if increased, discontinue use and seek medical advice.

Keep out of reach of children.

If swallowed, get medical help or contact a Poison Control Center right away.

Do not use

if you have very sensitive skin or are sensitive to salicylic acid.

DIRECTIONS

Apply 2-3 drops once a day where needed on clean skin. Avoid the eye area. Follow with Acne Balancing Cream.

OTHER INFORMATION

Store at room temperature.

INACTIVE INGREDIENTS

Water/Aqua, Propylene Glycol, Glycerin, Sodium PCA, Glycolic Acid, Acrylates/C10-30 Alkyl Acrylate Crosspolymer, Xanthan Gum, Hamamelis Virginiana Water, Dehydroacetic Acid, Benzyl Alcohol, Sodium Benzoate, Potassium Sorbate, Triethanolamine, Salix Alba Bark Water, Tocopheryl Acetate.

Questions or Comments?

info@farmasius.com Monday – Friday (9 a.m – 6 p.m. EST) (786) 238-7338